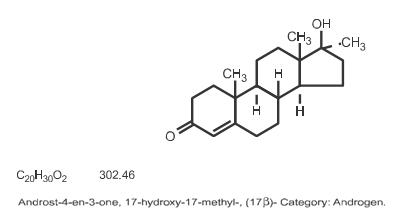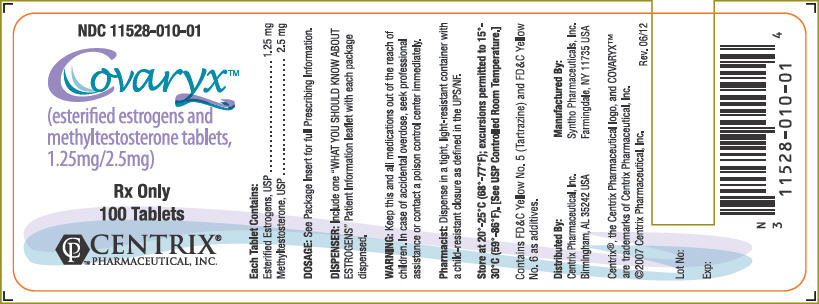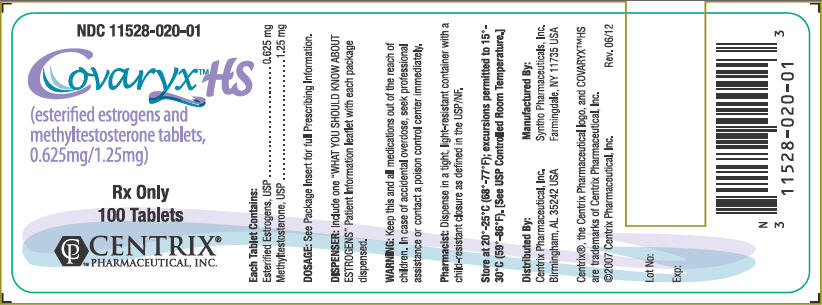 DRUG LABEL: COVARYX
NDC: 11528-020 | Form: TABLET, COATED
Manufacturer: CENTRIX PHARMACEUTICAL, INC,
Category: prescription | Type: HUMAN PRESCRIPTION DRUG LABEL
Date: 20200125
DEA Schedule: CIII

ACTIVE INGREDIENTS: ESTROGENS, ESTERIFIED 0.625 mg/1 1; METHYLTESTOSTERONE 1.25 mg/1 1
INACTIVE INGREDIENTS: TALC; ALUMINUM OXIDE; SILICON DIOXIDE; FD&C YELLOW NO. 6; FD&C YELLOW NO. 5; POLYETHYLENE GLYCOL, UNSPECIFIED; SODIUM BICARBONATE; SODIUM CITRATE; TITANIUM DIOXIDE; LACTOSE, UNSPECIFIED FORM; MAGNESIUM STEARATE; D&C RED NO. 30; MICROCRYSTALLINE CELLULOSE; POLYVINYL ALCOHOL, UNSPECIFIED

COVARYX

Warnings

1. ESTROGENS HAVE BEEN REPORTED TO INCREASE THE RISK OF ENDOMETRIAL CARCINOMA

Three independent case control studies have reported an increased risk of endometrial cancer in postmenopausal women exposed to exogenous estrogens for prolonged periods.1-3 This risk was independent of the other known risk factors for endometrial cancer. These studies are further supported by the finding that incidence rates of endometrial cancer have increased sharply since 1969 in eight different areas of the United States with population-based cancer reporting systems, an increase which may be related to the rapidly expanding use of estrogens during the last decade.4 The three case control studies reported that the risk of endometrial cancer in estrogen users was about 4.5 to 13.9 times greater than in nonusers. The risk appears to depend on both duration of treatment1 and on estrogen dose.4 In view of these findings, when estrogens are used for the treatment of menopausal symptoms, the lowest dose that will control symptoms should be utilized and medication should be discontinued as soon as possible. When prolonged treatment is medically indicated, the patient should be reassessed on at least a semiannual basis to determine the need for continued therapy. Although the evidence must be considered preliminary, one study suggests that cyclic administration of low doses of estrogen may carry less risk than continuous administration;3 it therefore appears prudent to utilize such a regimen. Close clinical surveillance of all women taking estrogens is important. In all cases of undiagnosed persistent or recurring abnormal vaginal bleeding, adequate diagnostic measures should be undertaken to rule out malignancy. There is no evidence at present that "natural" estrogens are more or less hazardous than "synthetic" estrogens at equiestrogenic doses.

2. ESTROGENS SHOULD NOT BE USED DURING PREGNANCY

The use of female sex hormones, both estrogens and progestogens, during early pregnancy may seriously damage the offspring. It has been shown that females exposed in utero to diethylstilbestrol, a non-steroidal estrogen, have an increased risk of developing in later life a form of vaginal or cervical cancer that is ordinarily extremely rare.5-6 This risk has been estimated as not greater than 4 per 1,000 exposures.7 Furthermore, a high percentage of such exposed women (from 30 to 90 percent) have been found to have vaginal adenosis,8-12 epithelial changes of the vagina and cervix. Although these changes are histologically benign, it is not known whether they are precursors of malignancy. Although similar data are not available with the use of other estrogens, it cannot be presumed they would not induce similar changes. Several reports suggest an association between intrauterine exposure to female sex hormones and congenital anomalies, including congenital heart defects and limb reduction defects.13-16

One case control study16 estimated a 4.7-fold increased risk of limb reduction defects in infants exposed in utero to sex hormones (oral contraceptives, hormone withdrawal tests for pregnancy, or attempted treatment for threatened abortion). Some of these exposures were very short and involved only a few days of treatment. The data suggest that the risk of limb reduction defects in exposed fetuses is somewhat less than 1 per 1,000. In the past, female sex hormones have been used during pregnancy in an attempt to treat threatened or habitual abortion. There is considerable evidence that estrogens are ineffective for these indications, and there is no evidence from well controlled studies that progestogens are effective for these uses. If COVARYX® or COVARYX® H.S. is used during pregnancy, or if the patient becomes pregnant while taking this drug, she should be apprised of the potential risks to the fetus, and the advisability of pregnancy continuation.

3. CARDIOVASCULAR AND OTHER RISKS

COVARYX® and COVARYX® H.S. Tablets do not contain a progestin. COVARYX® and COVARYX® H.S. Tablets are an Estrogen/Androgen product. Estrogens with or without progestins should not be used for the prevention of cardiovascular disease. The Women's Health Initiative (WHI) study reported increased risks of myocardial infarction, stroke, invasive breast cancer, pulmonary emboli, and deep vein thrombosis in postmenopausal women during 5 years of treatment with conjugated equine estrogens (CE 0.625 mg) combined with medroxyprogesterone acetate (MPA 2.5 mg) relative to placebo (See CLINICAL PHARMACOLOGY, Clinical Studies). Other doses of conjugated estrogens with medroxyprogesterone and other combinations of estrogens and progestins were not studied in the WHI and, in the absence of comparable data, these risks should be assumed to be similar. Because of these risks, estrogens with or without progestins should be prescribed at the lowest effective doses and for the shortest duration consistent with treatment goals and risks for the individual woman.

Description

COVARYX®: Each light yellow, capsule-shaped, film coated tablet debossed "C010" on obverse and plain on the reverse contains 1.25 mg of Esterified Estrogens, USP and 2.5 mg of Methyltestosterone, USP.

COVARYX® H.S. (Half-Strength): Each light pink, capsule-shaped, film coated tablet debossed "C020" on obverse and plain on the reverse contains 0.625 mg of Esterified Estrogens, USP and 1.25 mg of Methyltestosterone, USP.

Esterified Estrogens

Esterified Estrogens, USP is a mixture of the sodium salts of the sulfate esters of the estrogenic substances, principally estrone, that are of the type excreted by pregnant mares. Esterified Estrogens contain not less than 75.0 percent and not more than 85.0 percent of sodium estrone sulfate, and not less than 6.0 percent and not more than 15.0 percent of sodium equilin sulfate, in such proportion that the total of these two components is not less than 90.0 percent.

Category: Estrogens

Methyltestosterone

Methyltestosterone, USP is an androgen. Androgens are derivatives of cyclopentano-perhydrophenanthrene. Endogenous androgens are C-19 steroids with a side chain at C-17, and with two angular methyl groups.

Testosterone is the primary endogenous androgen. Fluoxymesterone and methyltestosterone are synthetic derivatives of testosterone. Methyltestosterone is a white to light yellow crystalline substance that is virtually insoluble in water but soluble in organic solvents. It is stable in air but decomposes in light. Methyltestosterone structural formula:

COVARYX® and COVARYX® H.S. Tablets contain the following inactive ingredients: Microcrystalline Cellulose, Colloidal Silicon Dioxide, Lactose, Sodium Bicarbonate, Sodium Citrate, Magnesium Stearate, Polyvinyl Alcohol, Polyethylene Glycol, Talc, Titanium Dioxide, FD&C Yellow #5 Tartrazine Aluminum Lake, FD&C Yellow #6 Sunset Yellow FCF Aluminum Lake, and D&C Red #30 Helendon Pink Aluminum Lake.

Clinical Pharmacology

Estrogens

Estrogens are important in the development and maintenance of the female reproductive system and secondary sex characteristics. They promote growth and development of the vagina, uterus, and fallopian tubes, and enlargement of the breasts. Indirectly, they contribute to the shaping of the skeleton, maintenance of tone and elasticity of urogenital structures, changes in the epiphyses of the long bones that allow for the pubertal growth spurt and its termination, growth of axillary and pubic hair, and pigmentation of the nipples and genitals. Decline of estrogenic activity at the end of the menstrual cycle can bring on menstruation, although the cessation of progesterone secretion is the most important factor in the mature ovulatory cycle. However, in the preovulatory or nonovulatory cycle, estrogen is the primary determinant in the onset of menstruation. Estrogens also affect the release of pituitary gonadotropins.

The pharmacologic effects of esterified estrogens are similar to those of endogenous estrogens. They are soluble in water and are well absorbed from the gastrointestinal tract.

In responsive tissues (female genital organs, breasts, hypothalamus, pituitary) estrogens enter the cell and are transported into the nucleus. As a result of estrogen action, specific RNA and protein synthesis occurs.

Estrogen Pharmacokinetics

Metabolism and inactivation occur primarily in the liver. Some estrogens are excreted into the bile; however they are reabsorbed from the intestine and returned to the liver through the portal venous system. Water soluble esterified estrogens are strongly acidic and are ionized in body fluids, which favor excretion through the kidneys since tubular reabsorption is minimal.

Androgens

Endogenous androgens are responsible for the normal growth and development of the male sex organs and for maintenance of secondary sex characteristics. These effects include the growth and maturation of prostate, seminal vesicles, penis, and scrotum; the development of male hair distribution, such as beard, pubic, chest, and axillary hair, laryngeal enlargement, vocal cord thickening, alterations in body musculature, and fat distribution. Drugs in this class also cause retention of nitrogen, sodium, potassium, phosphorus, and decreased urinary excretion of calcium. Androgens have been reported to increase protein anabolism and decrease protein catabolism. Nitrogen balance is improved only when there is sufficient intake of calories and protein. Androgens are responsible for the growth spurt of adolescence and for the eventual termination of linear growth which is brought about by fusion of the epiphyseal growth centers. In children, exogenous androgens accelerate linear growth rates, but may cause a disproportionate advancement in bone maturation. Use over long periods may result in fusion of the epiphyseal growth centers and terminaton of growth process. Androgens have been reported to stimulate the production of red blood cells by enhancing the production of erythropoietic stimulating factor.

Androgen Pharmacokinetics

Testosterone given orally is metabolized by the gut and 44 percent is cleared by the liver in the first pass. Oral doses as high as 400 mg per day are needed to achieve clinically effective blood levels for full replacement therapy. The synthetic androgens (methyltestosterone and fluoxymesterone) are less extensively metabolized by the liver and have longer half-lives. They are more suitable than testosterone for oral administration.

Testosterone in plasma is 98 percent bound to a specific testosterone-estradiol binding globulin, and about 2 percent is free. Generally, the amount of this sex-hormone binding globulin in the plasma will determine the distribution of testosterone between free and bound forms, and the free testosterone concentration will determine its half-life.

About 90 percent of a dose of testosterone is excreted in the urine as glucuronic and sulfuric acid conjugates of testosterone and its metabolites; about 6 percent of a dose is excreted in the feces, mostly in the unconjugated form. Inactivation of testosterone occurs primarily in the liver. Testosterone is metabolized to various 17-keto steroids through two different pathways. There are considerable variations of the half-life of testosterone as reported in the literature, ranging from 10 to 100 minutes. In many tissues the activity of testosterone appears to depend on reduction to dihydrotestosterone, which binds to cytosol receptor proteins. The steroid receptor complex is transported to the nucleus where it initiates transcription events and cellular changes related to androgen action.

Indications & Usage

COVARYXT® and COVARYX® H.S. are indicated in the treatment of

Moderate to severe vasomotor symptoms associated with the menopause in those patients not improved by estrogens alone. (There is no evidence that estrogens are effective for nervous symptoms or depression without associated vasomotor symptoms, and they should not be used to treat such conditions.)

COVARYXT® and COVARYX® H.S. HAVE NOT BEEN SHOWN TO BE EFFECTIVE FOR ANY PURPOSE DURING PREGNANCY AND ITS USE MAY CAUSE SEVERE HARM TO THE FETUS (See BOXED WARNINGS).

Contraindications

Estrogens should not be used in women with any of the following conditions:

1. Known or suspected cancer of the breast except in appropriately selected patients being treated for metastatic disease.
2. Known or suspected estrogen-dependent neoplasia.
3. Known or suspected pregnancy (See BOXED WARNINGS).
4. Undiagnosed abnormal genital bleeding.
5. Active thrombophlebitis or thromboembolic disorders.
6. A past history of thrombophlebitis, thrombosis, or thromboembolic disorders associated with previous estrogen use (except when in treatment of breast malignancy).

Methyltestosterone should not be used in:

1. The presence of severe liver damage.
2. Pregnancy and in breast-feeding mothers because of the possibility of masculinization of the female fetus or breast-fed infant.

Warnings

(See BOXED WARNINGS.)

Associated with Estrogens

1.Breast Cancer (See BOXED WARNINGS).

2.Induction of Malignant Neoplasms: Long-term continuous administration of natural and synthetic estrogens in certain animal species increases the frequency of carcinomas of the breast, cervix, vagina, and liver. There is now evidence that estrogens increase the risk of carcinoma of the endometrium in humans (See BOXED WARNINGS). At the present time there is no satis- factory evidence that estrogens given to postmenopausal women increase the risk of cancer of the breast,17 although a recent longterm follow-up of a single physician's practice has raised this possibility.18 Because of the animal data, there is a need for caution in prescribing estrogens for women with a strong family history of breast cancer or who have breast nodules, fibrocystic disease, or abnormal mammograms.

3.Cardiovascular Disorders: Estrogen with progestogen therapy has been associated with an increased risk of cardiovascular events such as myocardial infarction and stroke, as well as venous thrombosis and pulmonary embolism (venous thromboembolism or VTE). Should any of these occur or be suspected, estrogen with progestogens should be discontinued immediately. Risk factors for cardiovascular disease (e.g., hypertension, diabetes mellitus, tobacco use, hypercholesterolemia, and obesity) should be managed appropriately. If feasible, estrogens with progestins should be discontinued at least 4 to 6 weeks before surgery of the type associated with an increased risk of thromboembolism, or during periods of prolonged immobilization.

4.Gallbladder Disease: A recent study has reported a 2- to 3-fold increase in the risk of surgically confirmed gallbladder disease in women receiving postmenopausal estrogens,17 similar to the 2-fold increase previously noted in users of oral contraceptives.19-24
In the case of oral contraceptives the increased risk appeared after two years of use.24

5.Effects similar to those caused by estrogen-progestogen oral contraceptives: There are several serious adverse effects of oral contraceptives, most of which have not, up to now, been documented as consequences of postmenopausal estrogen therapy. This may reflect the comparatively low doses of estrogen used in postmenopausal women. It would be expected that the larger doses of estrogen used to treat prostatic or breast cancer or postpartum breast engorgement are more likely to result in these adverse effects, and, in fact, it has been shown that there is an increased risk of thrombosis in men receiving estrogens for prostatic cancer and women for postpartum breast engorgement. 20-23

Thromboembolic Disease: It is now well established that users of oral contraceptives have an increased risk of various thromboembolic and thrombotic vascular diseases, such as thrombophlebitis, pulmonary embolism, stroke, and myocardial infarction.24-31 Cases of retinal thrombosis, mesenteric thrombosis, and optic neuritis have been reported in oral contraceptive users.

There is evidence that the risk of several of these adverse reactions is related to the dose of the drug.32,33 An increased risk of postsurgery thromboembolic complications has also been reported in users of oral contraceptives.34,35 If feasible, estrogen should be discontinued at least 4 weeks before surgery of the type associated with an increased risk of thromboembolism, or during periods of prolonged immobilization. While an increased rate of thromboembolic and thrombotic disease in postmenopausal users of estrogens has not been found,18-36 this does not rule out the possibility that such an increase may be present or that subgroups of women who have underlying risk factors or who are receiving relatively large doses of estrogens may have increased risk. Therefore estrogens should not be used in persons with active thrombophlebitis or thromboembolic disorders, and they should not be used (except in treatment of malignancy) in persons with a history of such disorders in association with estrogen use. They should be used with caution in patients with cerebral vascular or coronary artery disease and only for those in whom estrogens are clearly needed. Large doses of estrogen (5 mg esterified estrogens per day), comparable to those used to treat cancer of the prostate and breast, have been shown in a large prospective clinical trial in men37 to increase the risk of nonfatal myocardial infarction, pulmonary embolism and thrombophlebitis. When estrogen doses of this size are used, any of the thromboembolic and thrombotic adverse effects associated with oral contraceptive use should be considered a clear risk. Hepatic Adenoma: Benign hepatic adenomas appear to be associated with the use of oral contraceptives.38-40 Although benign and rare, these may rupture and may cause death through intra abdominal hemorrhage. Such lesions have not yet been reported in association with other estrogen or progestogen preparations but should be considered in estrogen users having abdominal pain and tenderness, abdominal mass, or hypovolemic shock. Hepatocellular carcinoma has also been reported in women taking estrogen-containing oral contraceptives.30 The relationship of this malignancy to these drugs is not known at this time.

Elevated Blood Pressure: Increased blood pressure is not uncommon in women using oral contraceptives. There is now a report that this may occur with use of estrogens in the menopause41 and blood pressure should be monitored with estrogen use, especially if high doses are used.

Glucose Tolerance: A worsening of glucose tolerance has been observed in a significant percentage of patients of estrogen containing oral contraceptives. For this reason, diabetic patients should be carefully observed while receiving estrogens.

6.Hypercalcemia: Administration of estrogens may lead to severe hypercalcemia in patients with breast cancer and bone metastases. If this occurs, the drug should be stopped and appropriate measures taken to reduce the serum calcium level.

Associated with Methyltestosterone

In patients with breast cancer, androgen therapy may cause hypercalcemia by stimulating osteolysis. In this case the drug should be discontinued. Prolonged use of high doses of androgens has been associated with the development of peliosis hepatis and hepatic neoplasms including hepatocellular carcinoma. (See PRECAUTIONS-Carcinogenesis). Peliosis hepatis can be a life-threatening or fatal complication. Cholestatic hepatitis and jaundice occur with 17-alpha-alkylandrogens at a relatively low dose. If cholestatic hepatitis with jaundice appears or if liver function tests become abnormal, the androgen should be discontinued and the etiology should be determined. Drug-induced jaundice is reversible when the medication is discontinued. Edema with or without heart failure may be a serious complication in patients with preexisting cardiac, renal, or hepatic disease. In addition to discontinuation of the drug, diuretic therapy may be required.

Precautions

Associated with Estrogens

General Precautions

A complete medical and family history should be taken prior to the initiation of any estrogen therapy. The pretreatment and periodic physical examinations should include special reference to blood pressure, breasts, abdomen, and pelvic organs, and should include a Papanicolaou smear. As a general rule, estrogens should not be prescribed for longer than one year without another physical examination being performed.
Fluid retention-Because estrogens may cause some degree of fluid retention, conditions which might be influenced by this factor such as asthma, epilepsy, migraine, and cardiac or renal dysfunction, require careful observation.
Certain patients may develop undesirable manifestations of excessive estrogenic stimulation, such as abnormal or excessive uterine bleeding, mastodynia, etc.
Oral contraceptives appear to be associated with an increased incidence of mental depression.24 Although it is not clear whether this is due to the estrogenic or progestogenic component of the contraceptive, patients with a history of depression should be carefully observed.
Preexisting uterine leiomyomata may increase in size during estrogen use.
The pathologist should be advised of estrogen therapy when relevant specimens are submitted.
Patients with a past history of jaundice during pregnancy have an increased risk of recurrence of jaundice while receiving estrogen containing oral contraceptive therapy. If jaundice develops in any patient receiving estrogen, the medication should be discontinued while the cause is investigated.
Estrogens may be poorly metabolized in patients with impaired liver function and they should be administered with caution in such patients.
Because estrogens influence the metabolism of calcium and phosphorus, they should be used with caution in patients with metabolic bone diseases that are associated with hypercalcemia or in patients with renal insufficiency.
Because of the effects of estrogens on epiphyseal closure, they should be used judiciously in young patients in whom bone growth is not complete.
Certain endocrine and liver function tests may be affected by estrogen-containng oral contraceptives. The following similar changes may be expected with larger doses of estrogen:

a. Increased sulfobromophthalein retention.
b. Increased prothrombin and factors VII, VIII, IX and X; decreased antithrombin 3: increased norepinephrine induced platelet aggregability.
c. Increased thyroxine-binding globulin (TBG) leading to increased circulating total thyroid hormone, as measured by PBI, T4 by column, or T4 by radioimmunoassay. Free T3 resin uptake is decreased, reflecting the elevated TBG; free T4 concentration is unaltered.
d. Impaired glucose tolerance.
e. Decreased pregnanediol excretion.
f. Reduced response to metyrapone test.
g. Reduced serum folate concentration.
h. Increased serum triglyceride and phospholipid concentration.

Information for the Patient

(See INFORMATION FOR PATIENT after REFERENCES).

Pregnancy Category X

(See CONTRAINDICATIONS and BOXED WARNINGS).

Nursing Mothers

As a general principle, the administration of any drug to nursing mothers should be done only when clearly necessary since many drugs are excreted in human milk.

Associated with Methyltestosterone

General Precautions

Women should be observed for signs of virilization (deepening of the voice, hirsutism, acne, clitoromegaly, and menstrual irregularities). Discontinuation of drug therapy at the time of evidence of mild virilism is necessary to prevent irreversible virilization. Such virilization is usual following androgen use at high doses.
Prolonged dosage of androgen may result in sodium and fluid retention. This may present a problem, especially in patients with compromised cardiac reserve or renal disease.
Hypersensitivity may occur rarely.
PBI may be decreased in patients taking androgens.
Hypercalcemia may occur. If this does occur, the drug should be discontinued.

Information for the Patient

The physician should instruct patients to report any of the following side effects of androgens

Women: Hoarseness, acne, changes in menstrual periods, or more hair on the face.

All Patients: Any nausea, vomiting, changes in skin color or ankle swelling.

Laboratory Tests

Women with disseminated breast carcinoma should have frequent determination of urine and serum calcium levels during the course of androgen therapy (See WARNINGS).
Because of the hepatotoxicity associated with the use of 17-alpha alkylated androgens, liver function tests should be obtained periodically.
Hemoglobin and hematocrit should be checked periodically for polycythemia in patients who are receiving high doses of androgens.

Drug Interactions

Anticoagulants: C-17 substituted derivatives of testosterone, such as methandrostenolone, have been reported to decrease the anticoagulant requirements of patients receiving oral anticoagulants. Patients receiving oral anticoagulant therapy require close monitoring, especially when androgens are started or stopped.
Oxyphenbutazone: Concurrent administration of oxyphenbutazone and androgens may result in elevated serum levels of oxyphenbutazone.
Insulin: In diabetic patients, the metabolic effects of androgens may decrease blood glucose and insulin requirements.

Drug/Laboratory Test Interferences

Androgens may decrease levels of thyroxine-binding globulin, resulting in decreased T4 serum levels and increased resin uptake of T3 and T4. Free thyroid hormone levels remain unchanged, however, and there is no clinical evidence of thyroid dysfunction.

Carcinogenesis

Animal Data

Testosterone has been tested by subcutaneous injection and implantation in mice and rats. The implant induced cervical- uterine tumors in mice, which metastasized in some cases. There is suggestive evidence that injection of testosterone into some strains of female mice increases their susceptibility to hepatoma. Testosterone is also known to increase the number of tumors and decrease the degree of differentiation of chemically induced carcinomas of the liver in rats.

Human Data

There are rare reports of hepatocellular carcinoma in patients receiving long-term therapy with androgens in high doses. Withdrawal of the drugs did not lead to regression of the tumors in all cases. Geriatric patients treated with androgens may be at increased risk for the development of prostatic hypertrophy and prostatic carcinoma.

Pregnancy

Teratogenic Effects

Pregnancy Category X

(See CONTRAINDICATIONS).

Nursing Mothers

It is not known whether androgens are excreted in human milk. Because many drugs are excreted in human milk and because of the potential for serious adverse reactions in nursing infants from androgens, a decision should be made whether to discontinue nursing or to discontinue the drug, taking into account the importance of the drug to the mother.

Adverse Reactions

Associated with Estrogens

(See WARNINGS regarding induction of neoplasia, adverse effects on the fetus, increased incidence of gallbladder disease, and adverse effects similar to those of oral contraceptives, including thromboembolism). The following additional adverse reactions have been reported with estrogenic therapy, including oral contraceptives:

1.Genitourinary system: Breakthrough bleeding; spotting; change in menstrual flow; dysmenorrhea; premenstrual-like syndrome; amenorrhea during and after treatment; increase in size of urerine fibromyomata; vaginal candidiasis; change in cervical erosion and in degree of cervical secretion; cystitis-like syndrome.
2. Breasts: Tenderness: enlargement; secretion.
3. Gastrointestinal: Nausea; vomiting; abdominal cramps; bloating; cholestatic jaundice.
4. Skin: Chloasma or melasma which may persist when drug is discontinued; erythema multiforme; erythema nodosum; hemorrhagic eruption; loss of scalp hair; hirsutism.
5. Eyes: Steepening of corneal curvature; intolerance to contact lenses.
6. Central Nervous System: Headache, migraine, dizziness; mental depression; chorea.
7. Miscellaneous: Increase or decrease in weight; reduced carbohydrate tolerance; aggravation of porphyria; edema; changes in libido.

Associated with Methyltestosterone

1. Endocrine and Urogenital.

Female: The most common side effects of androgen therapy are amenorrhea and other menstrual irregularities, inhibition of gonadotropin secretion, and virilization, including deepening of the voice and clitoral enlargement. The latter usually is not reversible after androgens are discontinued. When administered to a pregnant woman androgens cause virilization of external genitalia of the female fetus.

2. Skin and Appendages: Hirsutism, male pattern of baldness, and acne.
3. Fluid and Electrolyte Disturbances: Retention of sodium, chloride, water, potassium, calcium, and inorganic phosphates.
4. Gastrointestinal: Nausea, cholestatic jaundice, alterations in liver function test, rarely hepatocellular neoplasms, and peliosis hepatis (See WARNINGS).
5. Hematologic: Suppression of clotting factors II, V, VII, and X, bleeding in patients on concomitant anticoagulant therapy, and polycythemia.
6. Nervous System. Increased or decreased libido, headache, anxiety, depression, and generalized paresthesia.
7. Metabolic: Increased serum cholesterol.
8. Miscellaneous: Inflammation and pain at the site of intramuscular injection or subcutaneous implantation of testosterone containing pellets, stomatitis with buccal preparatons, and rarely anaphylactoid reactions.

To report SUSPECTED ADVERSE REACTIONS, contact Syntho Pharmaceuticals or FDA at 1-800-FDA-1088 or www.fda.gov/medwatch

Overdosage

Numerous reports of ingestion of large doses of estrogen-containing oral contraceptives by young children indicate that serious ill effects do not occur. Overdosage of estrogen may cause nausea, and withdrawal bleeding may occur in females. There have been no reports of acute overdosage with the androgens.

Dosage & Administration

Given cyclically for short-term use only

For treatment of moderate to severe vasomotor symptoms associated with the menopause in patients not improved by estrogen alone. The lowest dose that will control symptoms should be chosen and medication should be discontinued as promptly as possible. Administration should be cyclic (e.g., three weeks on and one week off). Attempts to discontinue or taper medication should be made at three to six month intervals.

Usual Dosage Range

1 capsule-shaped tablet of COVARYX® (1.25 mg/2.5 mg) or 1 to 2 capsule shaped tablets of COVARYX® H.S. (0.625 mg/1.25 mg) daily as recommended by the physician. Treated patients with an intact uterus should be monitored closely for signs of endometrial cancer and appropriate diagnostic measures should be taken to rule out malignancy in the event of persistent or recurring abnormal vaginal bleeding.

How Supplied

COVARYX® is a combination of Esterified Estrogens and Methyltestosterone. COVARYX® is supplied in bottles of 100 Tablets. Each light yellow, capsule-shaped, film coated tablet debossed "C010" on obverse and plain on the reverse contains 1.25 mg of Esterified Estrogens, USP and 2.5 mg of Methyltestosterone, USP (NDC 11528-010-01).

COVARYX® H.S. (Half-Strength) is a combination of Esterified Estrogens and Methyltestosterone. COVARYX® H.S. is supplied in bottles of 100 Tablets. Each light pink, capsule-shaped, film coated tablet debossed "C020" on obverse and plain on the reverse contains 0.625 mg of Esterified Estrogens, USP and 1.25 mg of Methyltestosterone, USP (NDC 11528-020-01).

Store at 20º-25ºC (68º-77ºF); excursions permitted to 15º-30ºC (59º-86ºF).
[See USP Controlled Room Temperature.]

References

1. Ziel HK, et al. N Engl J Med. 1975;293:1167-1170.
2. Smith DC, et al. N Engl J Med. 1975;293:1164-1167.
3. Mack TM, et al. N Engl J Med. 1976;294:1262-1267.
4. Weiss NS, et al. N Engl J Med. 1976;294:1259-1262.
5. Herbst AL, et al. N Engl J Med. 1971;284:878-881.
6. Greenwald P, et al. N Engl J Med. 1971;285:390-392.
7. Lanier A, et al. Mayo Clin Proc. 1973;48:793-799.
8. Herbst A, et al. Obstet Gynecol. 1972;40:287-298.
9. Herbst A, et al. Am J Obstet Gynecol. 1974;118:607-615.
10. Herbst A, et al. N Engl J Med. 1975;292:334-339.
11. Stafl A, et al. Obstet Gynecol. 1974;43:118-128.
12. Sherman Al, et al. Obstet Gynecol. 1974;44:531-545.
13. Gal l, et al. Nature. 1967;216:83.
14. Levy EP, et al. Lancet. 1973;1:611.
15. Nora J, et al. Lancet. 1973;1:941-942.
16. Janerich DT, et al. N Engl J Med. 1974;291:697-700.
17. Boston Collaborative Drug Surveillance Program. N Engl J Med. 1974;290:15-19.
18. Hoover R, et al. N Engl J Med. 1976;295:401-405.
19. Boston Collaborative Drug Surveillance Program. Lancet.1973;1:1399-1404.
20. Daniel DG, et al. Lancet. 1967;2:287-289.
21. The Veterans Administration Cooperative Urological Research Group. J Urol. 1967;98:516-522.
22. Bailar JC, Lancet. 1967;2:560.
23. Blackard C, et al. Cancer. 1970;26:249-256.
24. Royal College of General Practitioners: J Coll Gen Practit. 1967;13:267-279.
25. Inman WHW, et al. Br Med J. 1968;2:193-199.
26. Vessey MP, et al. Br Med J. 1969;2:651-657.
27. Sartwell PE, et al. Am J Epidemiol. 1969;90:365-380.
28. Collaborative Group for the Study of Stroke in Young Women. N Engl J Med. 1973;288:871-878.
29. Collaborative Group for the Study of Stroke in Young Women. JAMA. 1975;231:718-722.
30. Mann Jl, et al. Br Med J. 1975;2:245-248.
31. Mann Jl. et al. Br Med J. 1975;2:241-245.
32. Inman WHW, et al. Br Med J. 1970;2:203-209.
33. Stolley PD, et al. Am J Epidemiol. 1975;102:197-208.
34. Vessey MP, et al. Br Med J. 1970;3:123-126.
35. Greene GR, et al. Am J Public Health. 1972;62:680-685.
36. Rosenberg L. et al. N Engl J Med. 1976;294:1256-1259.
37. Coronary Drug Project Research Group. JAMA. 1970;214:1303-1313.
38. Baum J, et al. Lancet. 1973;2:926-928.
39. Mays ET, et al. JAMA. 1976;235:730-732.
40. Edmondson HA, et al. N Engl J Med. 1976;294:470-472.
41. Pfeffer RI, et al. Am J Epidemiol. 1976;103:445-456.

Information for Patients

INFORMATION FOR THE PATIENT1

WHAT YOU SHOULD KNOW ABOUT ESTROGENS

Estrogens are female hormones produced by the ovaries. The ovaries make several different kinds of estrogens. In addition, scientists have been able to make a variety of synthetic estrogens. As far as we know, all these estrogens have similar properties and therefore much the same usefulness, side effects, and risks. This leaflet is intended to help you understand what estrogens are used for, the risks involved in their use, and how to use them as safely as possible. This leaflet includes the most important information about estrogens, but not all the information. If you want to know more, you can ask your doctor or pharmacist to let you read the package insert prepared for the doctor.

USES OF ESTROGEN

Estrogens are prescribed by doctors for a number of purposes, including:

1. To provide estrogen during a period of adjustment when a woman's ovaries no longer produce it, in order to prevent certain uncomfortable symptoms of estrogen deficiency. (All women normally stop producing estrogens, generally between the ages of 45 and 55; this is called the menopause).
2. To prevent symptoms of estrogen deficiency when a woman's ovaries have been removed surgically before the natural menopause.
3. To prevent pregnancy. (Estrogens are given along with a progestogen, another female hormone; these combinations are called oral contraceptives or birth control pills. Patient labeling is available to women taking oral contraceptives and they will not be discussed in this leaflet.)
4. To treat certain cancers in women and men.

THERE IS NO PROPER USE OF ESTROGENS IN A PREGNANT WOMAN.

ESTROGENS IN THE MENOPAUSE

In the natural course of their lives, all women eventually experience a decrease in estrogen production. This usually occurs between ages 45 and 55 but may occur earlier or later. Sometimes the ovaries may need to be removed before narural menopause by an operation, producing a "surgical menopause."

When the amount of estrogen in the blood begins to decrease, many women may develop typical symptoms: Feelings of warmth in the face, neck, and chest of sudden intense episodes of heat and sweating throughout the body (called "hot flashes" or "hot flushes"). These symptoms are sometimes very uncomfortable. A few women eventually develop changes in the vagina (called "atrophic vaginitis") which cause discomfort, especially during and after intercourse.

Estrogens can be prescribed to treat these symptoms of the menopause. It is estimated that considerably more than half of all women undergoing the menopause have only mild symptoms or no symptoms at all and therefore do not need estrogens. Other women may need estrogens for a few months, while their bodies adjust to lower estrogen levels. Sometimes the need will be for periods longer than six months. In an attempt to avoid overstimulation of the uterus (womb), estrogens are usually given cyclically during each month of use, that is three weeks of pills followed by one week without pills.

Sometimes women experience nervous symptoms or depression during menopause. There is no evidence that estrogens are effective for such symptoms and they should not be used to treat them, although other treatment may be needed. You may have heard that taking estrogens for long periods (years) after the menopause will keep your skin soft and supple and keep you feeling young. There is no evidence that this is so, however, and such long-term treatment carries important risks.

THE DANGERS OF ESTROGENS

1.Cancer of the Uterus:

If estrogens are used in the postmenopausal period for more than a year, there is an increased risk of endometrial cancer (cancer of the uterus). Women taking estrogens have roughly 5 to 10 times as great a chance of getting this cancer as women who take no estrogens. To put this another way, while a postmenopausal woman not taking estrogens has 1 chance in 1,000 each year of getting cancer of the uterus, a woman taking estrogens has 5 to 10 chances in 1,000 each year.

For this reason it is important to take estrogens only when you really need them.

The risk of this cancer is greater the longer estrogens are used and also seems to be greater when larger doses are taken. For this reason, it is important to take the lowest dose of estrogen that will control symptoms and to take it only as long as it is needed. If estrogens are needed for longer periods of time, your doctor will want to reevaluate your need for estrogens at least every six months.

Women using estrogens should report any irregular vaginal bleeding to their doctors; such bleeding may be of no importance, but it can be an early warning of cancer of the uterus. If you have undiagnosed vaginal bleeding, you should not use estrogens until a diagnosis is made and you are certain there is no cancer of the uterus.

2.Other Possible Cancers: Estrogens can cause development of other tumors in animals, such as tumors of the breast, cervix, vagina, or liver, when given for a long time. This is a further reason to use estrogens only when clearly needed. While you are taking estrogens, it is important that you go to your doctor at least once a year for a physical examination. Also, if members of your family have had breast cancer or if you have breast nodules or abnormal mammograms (breast x-rays), your doctor may wish to carry out more frequent examinations of your breasts.

3.Gallbladder Disease: Women who use estrogens after menopause are more likely to develop gallbladder disease needing surgery as women who do not use estrogens. Birth control pills have a similar effect.

4.Abnormal Blood Clotting: Oral contraceptives increase the risk of blood clotting in various parts of the body. This can result in a stroke (if the clot is in the brain), a heart attack (clot in a blood vessel of the heart), or pulmonary embolus (a clot which forms in the legs or pelvis, then breaks off and travels to the lungs). Any of these can be fatal. At this time use of estrogens in the menopause is not known to cause such blood clotting, but this has not been fully studied and there could still prove to be such a risk. It is recommended that if you have had clotting in the legs or lungs or a heart attack or stroke while you were using estrogens or birth control pills, you should not use estrogens (unless they are being used to treat cancer of the breast or prostate). If you have had a stroke or heart attack or if you have angina pectoris, estrogens should be used with great caution and only if clearly needed (for example, if you have severe symptoms of the menopause). The larger doses of estrogen used to prevent swelling of the breasts after pregnancy have been reported to cause clotting in the legs and lungs.

5.Other Potential Risks: Using estrogens and progestins may increase your chances of getting heart attacks, strokes, breast cancer, or blood clots.

SPECIAL WARNING ABOUT PREGNANCY

You should not receive estrogen if you are pregnant. If this should occur, there is a greater than usual chance that the developing child will be born with a birth defect, although the possibility remains fairly small. A female child may have an increased risk of developing cancer of the vagina or cervix later in life (in the teens or twenties). Every possible effort should be made to avoid exposure to estrogens during pregnancy. If exposure occurs, see your doctor.

OTHER EFFECTS OF ESTROGENS

In addition to the serious known risks of estrogens described above, estrogens have the following side effects and potential risks:

1. Nausea and vomiting: The most common side effect of estrogen therapy is nausea. Vomiting is less common.
2. Effects on breasts: Estrogens may cause breast tenderness or enlargement and may cause the breasts to secrete a liquid. These effects are not dangerous.
3. Effects on the uterus: Estrogens may cause benign fibroid tumors of the uterus to get larger. Some women will have menstrual bleeding when estrogens are stopped. But if the bleeding occurs on days you are still taking estrogens you should report this to your doctor.
4. Effects on liver: Women taking oral contraceptives develop on rare occasions a benign tumor of the liver which can rupture and bleed into the abdomen. So far, these tumors have not been reported in women using estrogens in the menopause, but you should report any swelling or unusual pain or tenderness in the abdomen to your doctor immediately. Women with a past history of jaundice (yellowing of the skin and white parts of the eyes) may get jaundice again during estrogen use. If this occurs, stop taking estrogens and see your doctor.
5. Other effects: Estrogens may cause excess fluid to be retained in the body. This may make some conditions worse, such as epilepsy, migraine, heart disease, or kidney disease.

SUMMARY

Estrogens have important uses, but they have serious risks as well. You must decide, with your doctor, whether the risks are acceptable to you in view of the benefits of the treatment. Except where your doctor has prescribed estrogens for use in special cases of cancer of the breast or prostate, you should not use estrogens if you have cancer of the breast or uterus, are pregnant, have undiagnosed abnormal vaginal bleeding, or have had a stroke, heart attack or angina, or clotting in the legs or lungs in the past while you were taking estrogens.

You can use estrogens as safely as possible by understanding that your doctor will require regular physical examinations while you are taking them and will try to discontinue the drug as soon as possible and use the smallest dose possible. Be alert for signs of trouble including:

1. Abnormal bleeding from the vagina.
2. Pains in the calves or chest or sudden shortness of breath, or coughing blood (indicating possible clots in the legs, heart, or lungs).
3. Severe headache, dizziness, faintness, or changes in vision (indicating possible developing clots in the brain or eye).
4. Breast lumps (you should ask your doctor how to examine your own breasts).
5. Jaundice (yellowing of the skin).
6. Mental depression.

Based on his or her assessment of your medical needs, your doctor has prescribed this drug for you. Do not give the drug to anyone else.

1
This product has not obtained FDA pre-market approval applicable for new drugs.

How Supplied

COVARYX® is a combination of Esterified Estrogens and Methyltestosterone. COVARYX® is supplied in bottles of 100 Tablets. Each light yellow, capsule-shaped, film coated tablet debossed "C010" on obverse and plain on the reverse contains 1.25 mg of Esterified Estrogens, USP and 2.5 mg of Methyltestosterone, USP.

COVARYX® H.S. (Half-Strength) is a combination of Esterified Estrogens and Methyltestosterone. COVARYX® H.S. is supplied in bottles of 100 Tablets. Each light pink, capsule-shaped, film coated tablet debossed "C020" on obverse and plain on the reverse contains 0.625 mg of Esterified Estrogens, USP and 1.25 mg of Methyltestosterone, USP.

Store at 20º-25ºC (68º-77ºF); excursions permitted to 15º-30ºC (59º-86ºF).
[See USP Controlled Room Temperature.]

Distributed by:

Centrix Pharmaceutical, Inc.
Birmingham, AL 35242 USA

Manufactured by:
ANDAPharm, LLC
Ft. Lauderdale, FL 33309 USA

CENTRIX®, the Centrix Pharmaceutical logo, and COVARYX® are registered trademarks of Centrix Pharmaceutical, Inc.

©2007 Centrix Pharmaceutical, Inc.

Iss.04/07

1.25mg/2.5mg Tablet Bottle Label

NDC 11528-010-01

Covaryx™
(esterified estrogens and
methyltestosterone tablets,
1.25mg/2.5mg)

Rx Only
100 Tablets

CP™ CENTRIX®
PHARMACEUTICAL, INC.

0.625mg/1.25mg Tablet Bottle Label

NDC 11528-020-01

Covaryx™HS
(esterified estrogens and
methyltestosterone tablets,
0.625mg/1.25mg)

Rx Only
100 Tablets

CP™ CENTRIX®
PHARMACEUTICAL, INC.